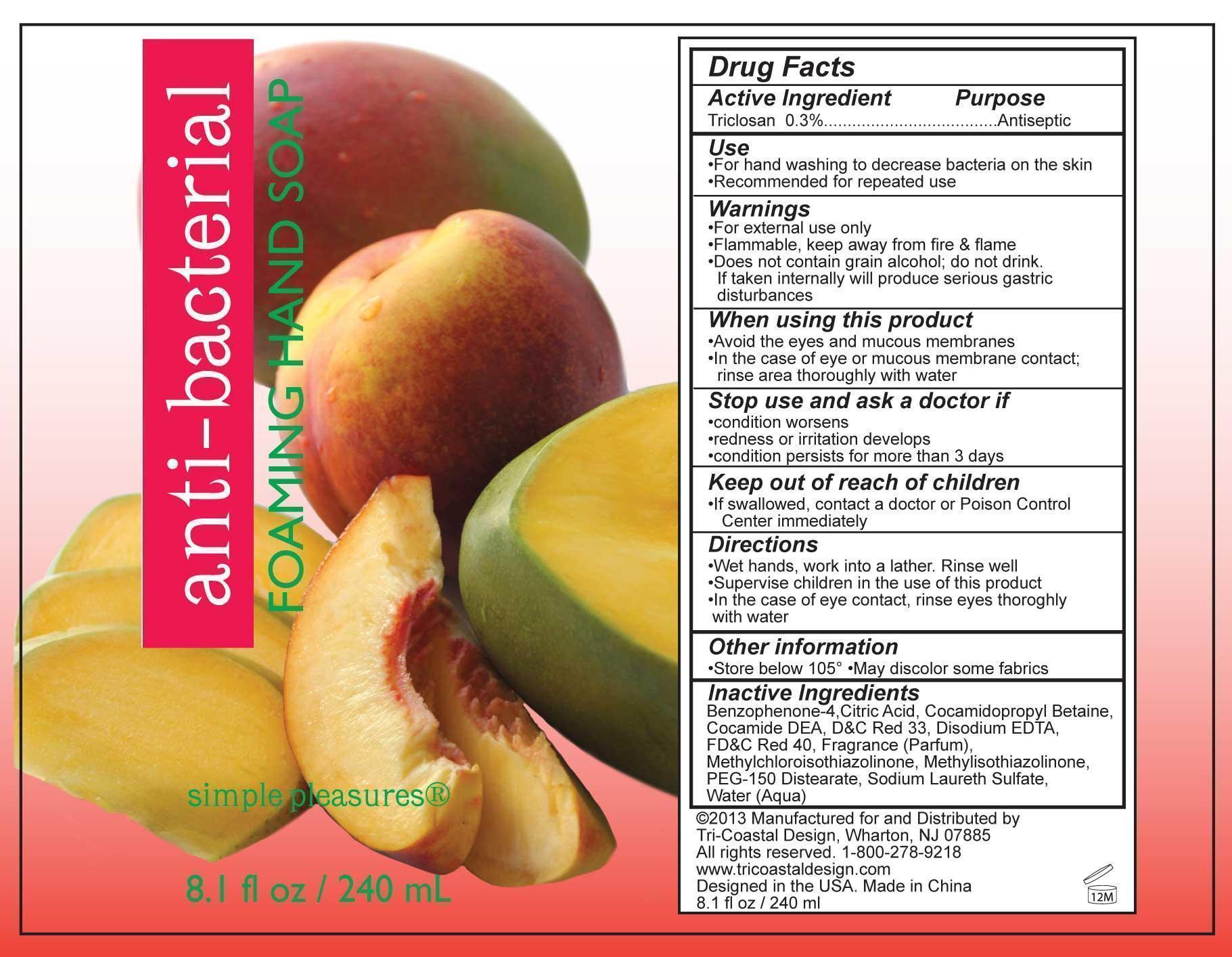 DRUG LABEL: simple pleasures
NDC: 49852-174 | Form: SOAP
Manufacturer: Tri-Coastal Design Company Inc. 
Category: otc | Type: HUMAN OTC DRUG LABEL
Date: 20121004

ACTIVE INGREDIENTS: TRICLOSAN 0.3 g/100 mL
INACTIVE INGREDIENTS: BENZOPHENONE; CITRIC ACID MONOHYDRATE; COCAMIDOPROPYL BETAINE; COCO DIETHANOLAMIDE; D&C RED NO. 33; EDETATE DISODIUM; FD&C RED NO. 40; METHYLCHLOROISOTHIAZOLINONE; METHYLISOTHIAZOLINONE; PEG-150 DISTEARATE; SODIUM LAURETH SULFATE; WATER

Drug Facts

Active Ingredient

Triclosan 0.3%

Purpose

Antiseptic

Uses

- For handwashing to decrease bacteria on the skin
- Recommended for repeated use

Warnings

- For external use only
- Flammable, keep away from fire and flame
- Does not contain grain alcohol; do not drink.

If taken internally will produce serious gastric disturbances

When using this product

- Avoid the eyes and mucous membranes
- In the case of eye or mucous membrane contact; rinse area thoroughly with water

Stop use and ask a doctor if

- condition worsens
- redness or irritation develops
- condition persists for more than 3 days

Keep out of reach of children

If swallowed contact a doctor or Poison Control Center immediately.

Directions

- Wet hands, work into a lather. Rinse well
- Supervise children in the use of this product
- In the case of eye contact, rinse eyes thoroughly with water

Other information

- Store below 105F
- May discolor some fabrics

Inactive Ingredients

Benzophenone-4, Citric Acid, Cocamidopropyl Betaine, Cocamide DEA, DC Red 33, Disodium EDTA, FDC Red 40, Fragrance (Parfum), Methylchloroisothiazolinone, Methylisothiazolinone, PEG-150 Distearate, Sodium Laureth Sulfate, Water (Aqua)